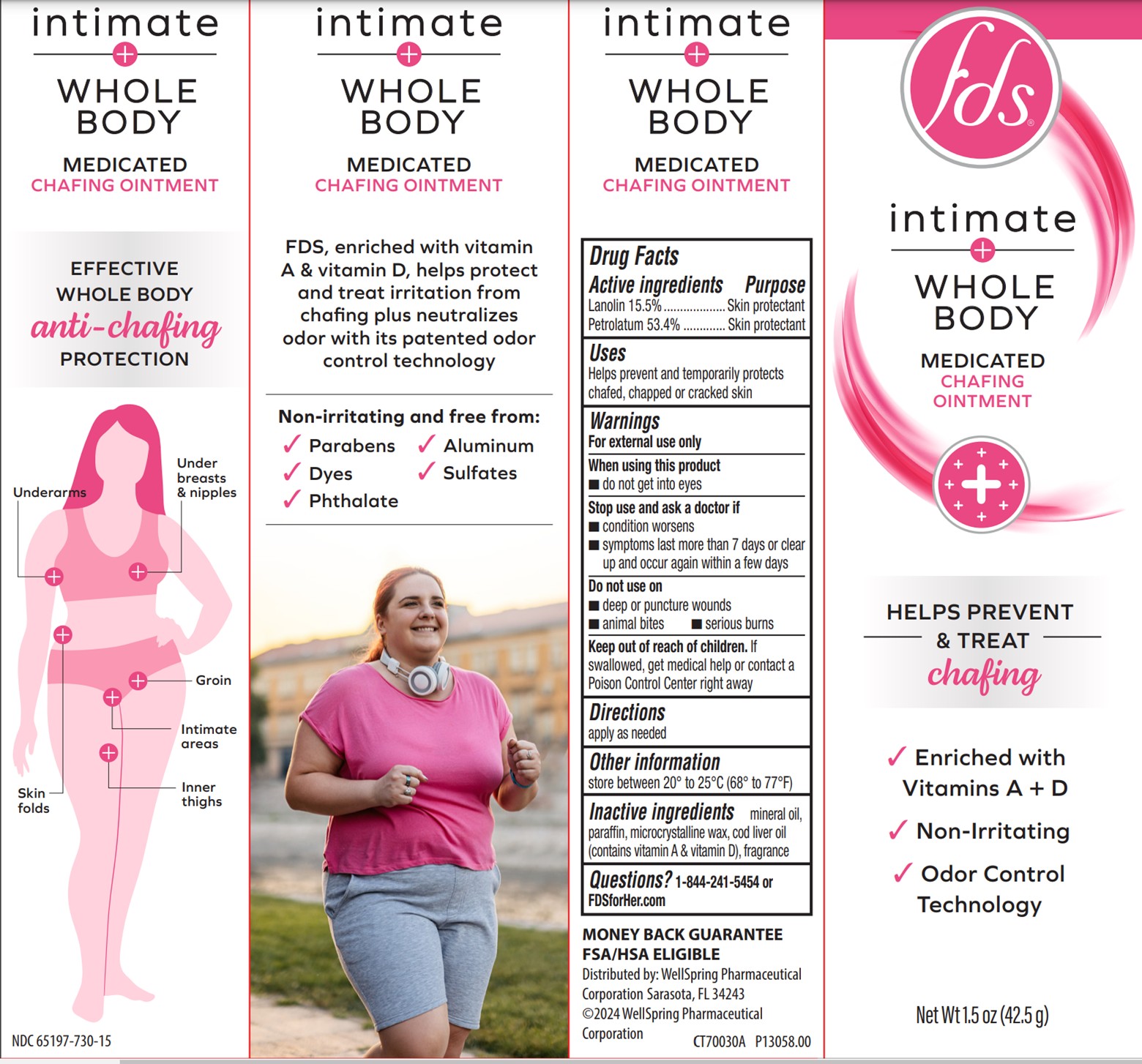 DRUG LABEL: FDS intimate Whole Body Medicated Chafing
NDC: 65197-730 | Form: OINTMENT
Manufacturer: WellSpring Pharmaceutical Corporation
Category: otc | Type: HUMAN OTC DRUG LABEL
Date: 20250203

ACTIVE INGREDIENTS: LANOLIN 15.5 g/100 g; PETROLATUM 53.4 g/100 g
INACTIVE INGREDIENTS: MINERAL OIL; PARAFFIN; MICROCRYSTALLINE WAX; COD LIVER OIL

FDS intimate Whole Body Medicated Chafing Ointment 1.5 oz (42.5g)

Active Ingredients

Lanolin 15.5%

Petrolatum 53.4%

Purpose

Skin protectant

Skin protectant

Uses

- Helps prevent and temporarily protects chafed, chapped or cracked skin

Warnings

For external use only

When using this product

- do not get into eyes

Stop use and ask a doctor if

- condition worsens
- symptoms last more than 7 days or clear up and occur again within a few days

Do not use on

- deep or puncture wounds
- animal bites
- serious burns

Keep out of reach of children

- If swallowed, get medical help or contact a Poison Control Center right away.

Directions

apply as needed

Other information

store between 20° to 25°C (68° to 77°F)

Inactive ingredients

mineral oil, paraffin, microcrystalline wax, cod liver oil (contains vitamin A & vitamin D), fragrance

Questions?

1-844-241-5454 or FDSforHer.com

Distributed by:

WellSpring Pharmaceutical Corporation
Sarasota, FL 34243

© 2024 WellSpring Pharmaceutical Corporation

PACKAGE LABEL. PRINCIPAL DISPLAY PANEL

FDS intimate Whole Body Medicated Chafing Ointment 1.5 oz (42.5g)

HELPS PREVENT AND TREAT Chafing

Enriched with Vitamins A+D

Non-Irritating

Odor Control Technology

NET WT 1.5 oz (42.5g)

CT70030A

NDC# 65197-730-15

P13058.00

FDS intimate Whole Body Medicated Chafing Ointment1.5 oz (42.5g)